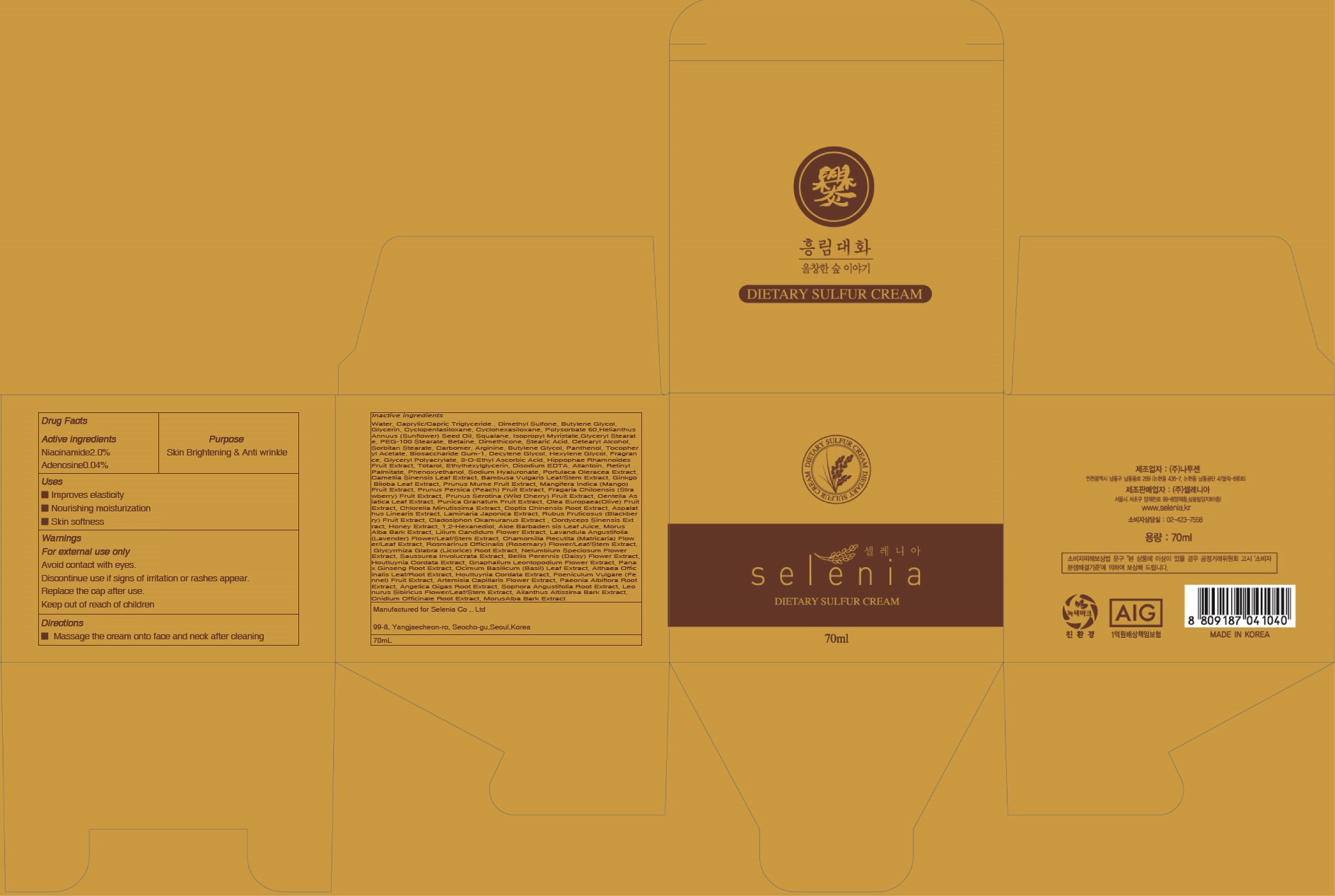 DRUG LABEL: SULFUR
NDC: 71946-020 | Form: CREAM
Manufacturer: Selenia
Category: otc | Type: HUMAN OTC DRUG LABEL
Date: 20191211

ACTIVE INGREDIENTS: Niacinamide 1.4 g/70 mL; Adenosine 0.02 g/70 mL
INACTIVE INGREDIENTS: Water; Butylene Glycol

ACTIVE INGREDIENT

Active ingredients: Niacinamide 2.0%, Adenosine 0.04%

INACTIVE INGREDIENT

Inactive ingredients: Water, Caprylic/Capric Triglyceride , Dimethyl Sulfone, Butylene Glycol, Glycerin, Cyclopentasiloxane, Cyclohexasiloxane, Polysorbate 60, Helianthus Annuus (Sunflower) Seed Oil, Squalane, Isopropyl Myristate, Glyceryl Stearate, PEG-100 Stearate, Betaine, Dimethicone, Stearic Acid, Cetearyl Alcohol, Sorbitan Stearate, Carbomer, Arginine, Butylene Glycol, Panthenol, Tocopheryl Acetate, Biosaccharide Gum-1, Decylene Glycol, Hexylene Glycol, Fragrance, Glyceryl Polyacrylate, 3-O-Ethyl Ascorbic Acid, Hippophae Rhamnoides Fruit Extract, Totarol, Ethylhexylglycerin, Disodium EDTA, Allantoin, Retinyl Palmitate, Phenoxyethanol, Sodium Hyaluronate, Portulaca Oleracea Extract, Camellia Sinensis Leaf Extract, Bambusa Vulgaris Leaf/Stem Extract, Ginkgo Biloba Leaf Extract, Prunus Mume Fruit Extract, Mangifera Indica (Mango) Fruit Extract, Prunus Persica (Peach) Fruit Extract, Fragaria Chiloensis (Strawberry) Fruit Extract, Prunus Serotina (Wild Cherry) Fruit Extract, Centella Asiatica Leaf Extract, Punica Granatum Fruit Extract, Olea Europaea (Olive) Fruit Extract, Chlorella Minutissima Extract, Coptis Chinensis Root Extract, Aspalathus Linearis Extract, Laminaria Japonica Extract, Rubus Fruticosus (Blackberry) Fruit Extract, Cladosiphon Okamuranus Extract , Cordyceps Sinensis Extract, Honey Extract, 1,2-Hexanediol, Aloe Barbadensis Leaf Juice, Morus Alba Bark Extract, Lilium Candidum Flower Extract, Lavandula Angustifolia (Lavender) Flower/Leaf/Stem Extract, Chamomilla Recutita (Matricaria) Flower/Leaf Extract, Rosmarinus Officinalis (Rosemary) Flower/Leaf/Stem Extract, Glycyrrhiza Glabra (Licorice) Root Extract, Nelumbium Speciosum Flower Extract, Saussurea Involucrata Extract, Bellis Perennis (Daisy) Flower Extract, Houttuynia Cordata Extract, Gnaphalium Leontopodium Flower Extract, Panax Ginseng Root Extract, Ocimum Basilicum (Basil) Leaf Extract, Althaea Officinalis Leaf/Root Extract, Houttuynia Cordata Extract, Foeniculum Vulgare (Fennel) Fruit Extract, Artemisia Capillaris Flower Extract, Paeonia Albiflora Root Extract, Angelica Gigas Root Extract, Sophora Angustifolia Root Extract, Leonurus Sibiricus Flower/Leaf/Stem Extract, Ailanthus Altissima Bark Extract, Cnidium Officinale Root Extract, Morus Alba Bark Extract

PURPOSE

Purpose: Skin Brightening & Anti wrinkle

WARNINGS

Warnings: For external use only Avoid contact with eyes. Discontinue use if signs of irritation or rashes appear. Replace the cap after use. Keep out of reach of children

KEEP OUT OF REACH OF CHILDREN

Uses

- Improves elasticity

- Nourishing moisturization

- Skin softness

Directions

Massage the cream onto face and neck after cleaning.